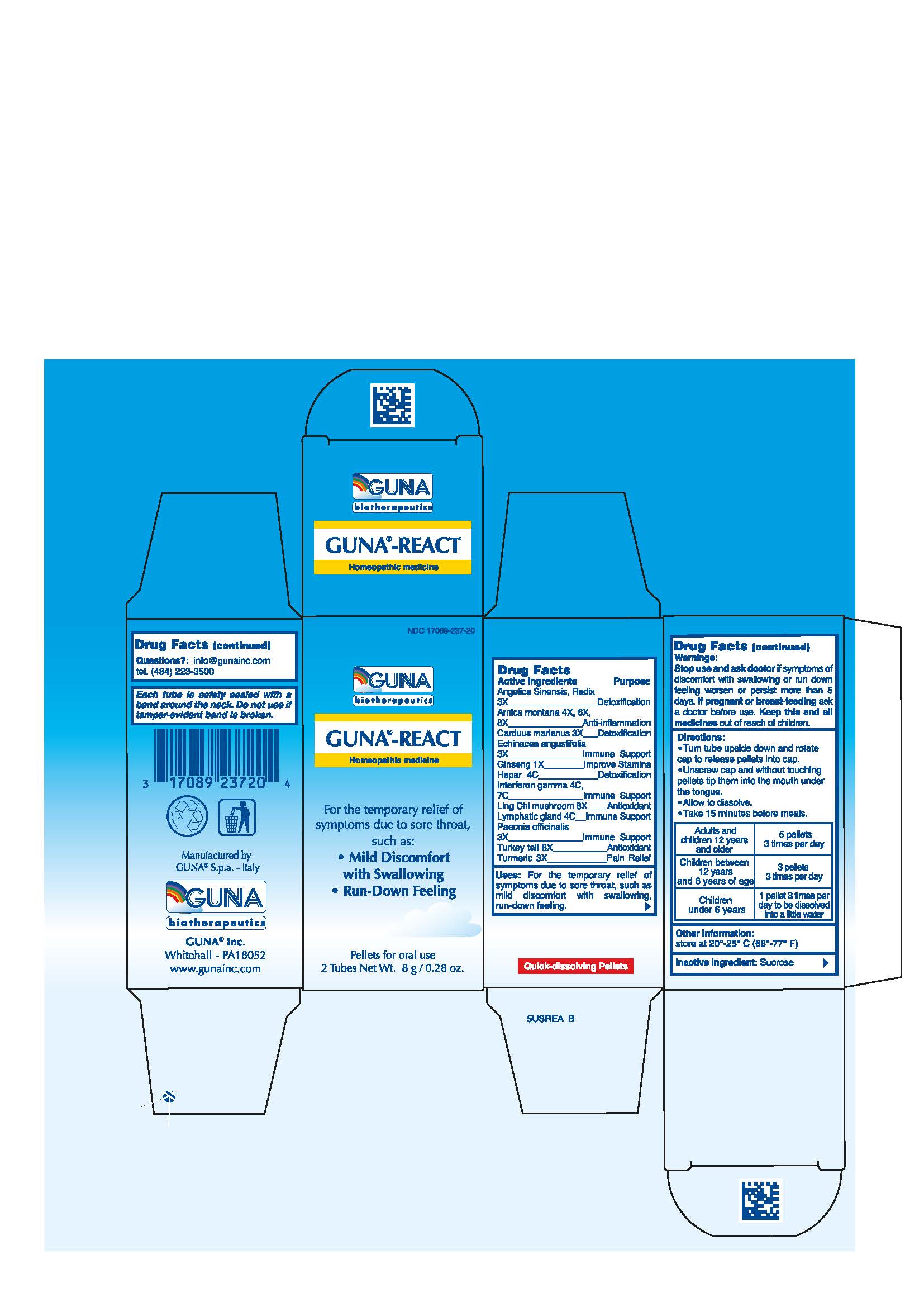 DRUG LABEL: GUNA-REACT
NDC: 17089-237 | Form: PELLET
Manufacturer: Guna spa
Category: homeopathic | Type: HUMAN OTC DRUG LABEL
Date: 20181221

ACTIVE INGREDIENTS: TURMERIC 3 [hp_X]/4 g; ANGELICA SINENSIS ROOT 3 [hp_X]/4 g; ARNICA MONTANA 4 [hp_X]/4 g; SILYBUM MARIANUM SEED 3 [hp_X]/4 g; ECHINACEA ANGUSTIFOLIA 3 [hp_X]/4 g; ASIAN GINSENG 1 [hp_X]/4 g; PORK LIVER 4 [hp_C]/4 g; INTERFERON GAMMA-1B 4 [hp_C]/4 g; REISHI 8 [hp_X]/4 g; SUS SCROFA SMALL INTESTINE MUCOSA LYMPH FOLLICLE 4 [hp_C]/4 g; PAEONIA OFFICINALIS ROOT 3 [hp_X]/4 g; FOMITOPSIS PINICOLA FRUITING BODY 8 [hp_X]/4 g
INACTIVE INGREDIENTS: SUCROSE 3.5 g/4 g

GUNA-REACT

ACTIVE INGREDIENTS/PURPOSE

ANGELICA SINENSIS, RADIX 3X DETOXIFICATION
ARNICA MONTANA 4X, 6X, 8X ANTI-INFLAMMATION
CARDUUS MARIANUS 3X DETOXIFICATION
ECHINACEA ANGUSTIFOLIA 3X IMMUNE SUPPORT
GINSENG 1X IMPROVE STAMINA
HEPAR 4C DETOXIFICATION
INTERFERON GAMMA 4C 7C IMMUNE SUPPORT
LING CHI MUSHROOM 8X ANTIOXIDANT
LYMPHATIC GLAND 4C IMMUNE SUPPORT
PAEONIA OFFICINALIS 3X IMMUNE SUPPORT
TURKEY TAIL 8X ANTIOXIDANT
TURMERIC 3X PAIN RELIEF

USES

For the temporary relief of symptoms due to sore throat, such as: •Mild Discomfort with Swallowing •Run-Down Feeling

WARNINGS

Stop use and ask doctor if symptoms of discomfort with swallowing or run down feeling worsen or persist more than 5 days

PREGNANCY

If pregnant or breast-feeding ask a health professional before use.

WARNINGS

Keep this and all medicines out of reach of children

DIRECTIONS

Take 15 minutes before meals
Adults and children 12 years and older 5 pellets 3 times per day
Children between 12 years and 6 years of age 3 pellets 3 times per day
Children under 6 years 1 pellet 3 times per day to be dissolved into a little water

QUESTIONS

Questions?: info@gunainc.com
tel. (484) 223-3500

Directions:

Turn tube upside down and rotate cap to release pellets into cap.
Unscrew cap and without touching pellets tip them into the mouth under the tongue.
Allow to dissolve
Take 15 minutes before meals.

Inactive ingredient: Sucrose.